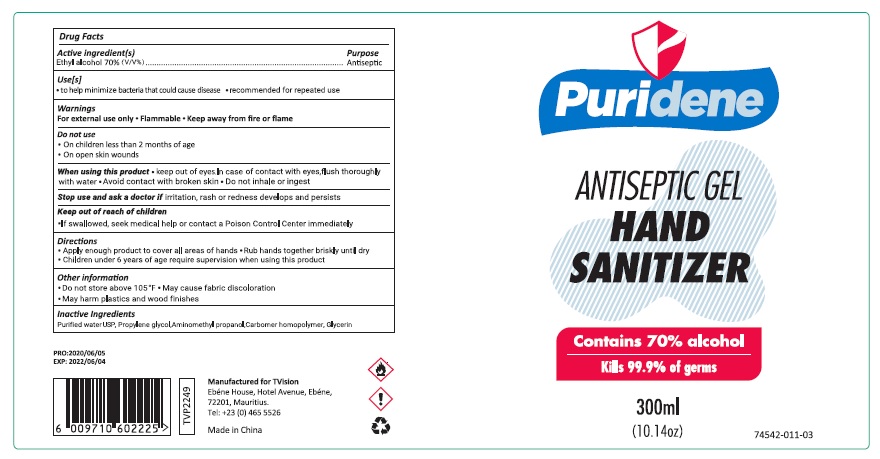 DRUG LABEL: PURIDENE
NDC: 74542-012 | Form: GEL
Manufacturer: Ningbo SKL International Co.,Ltd.
Category: otc | Type: HUMAN OTC DRUG LABEL
Date: 20200521

ACTIVE INGREDIENTS: ALCOHOL 70 mL/100 mL
INACTIVE INGREDIENTS: WATER; PROPYLENE GLYCOL; AMINOMETHYLPROPANOL; CARBOMER HOMOPOLYMER, UNSPECIFIED TYPE; GLYCERIN

PURIDENE WATERLESS HAND SANITIZER

Active Ingredient

Ethyl Alcohol 70%

Purpose

Antiseptic

Warnings

For external use only
Flammable
Keep away from fire or flame

When using this product:

- Keep out of eyes. In case of contact with eyes, flush thoroughly with water.
- Avoid contact with broken skin.
- Do not inhale or ingest

Stop use and ask a doctor if: irritation, rash or redness develops and persists.

Keep out of reach of children

If swallowed, seek medical help or contact a Poison Control Center immediately.

Directions

Apply enough product to cover all areas of hands.

Rub hands together briskly until dry.

Children under 6 years of age require supervision when using this product.

Uses

To help minimize bacteria on the skin that could cause disease.

Recommended for repeated use.

Other Information

Do not store above 105°F.

May cause fabric discoloration.

May harm plastic and wood finishes.

Inactive ingredient

Perified water, Propylene glycol, Aminomethyl propanol, Carbomer homopolymer, Glycerin